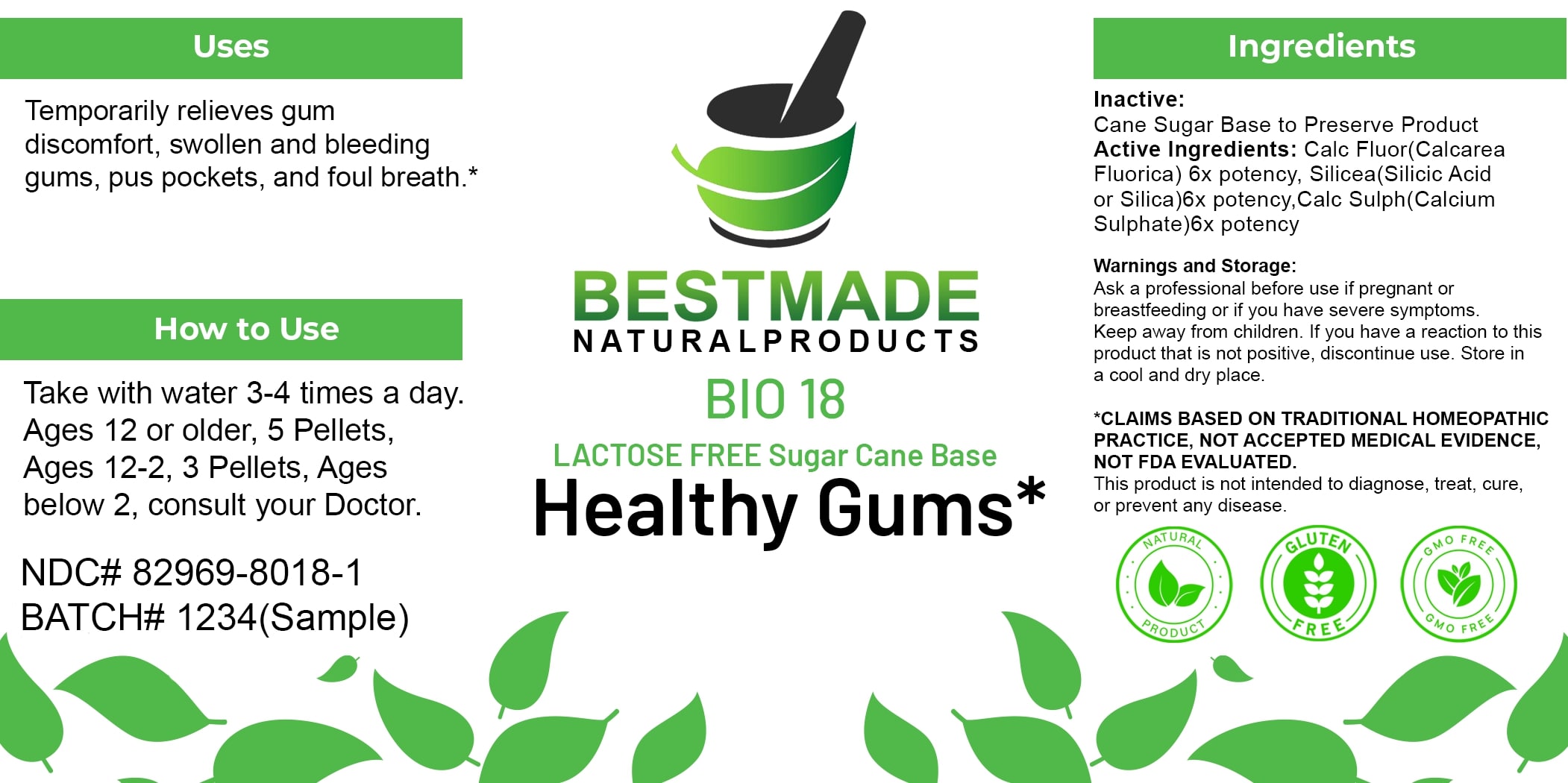 DRUG LABEL: Bestmade Natural Products BIO18 Lactose Free
NDC: 82969-8018 | Form: TABLET, SOLUBLE
Manufacturer: Bestmade Natural Products
Category: homeopathic | Type: HUMAN OTC DRUG LABEL
Date: 20250313

ACTIVE INGREDIENTS: CALCIUM FLUORIDE 6 [hp_X]/6 [hp_X]; CALCIUM SULFATE ANHYDROUS 6 [hp_X]/6 [hp_X]; SILICA 6 [hp_X]/6 [hp_X]
INACTIVE INGREDIENTS: SUCROSE 6 [hp_X]/6 [hp_X]

BIO18 Healthy Gums* LACTOSE FREE Sugar Cane Base

DOSAGE AND ADMINISTRATION

How to Use

Take with water 3-4 times a day. Ages 12 or older, 5 Pellets, Ages 12-2, 3 Pellets, Ages below 2, consult your Doctor.

Active Ingredients:

Calc Fluor (Calcarea Fluorica) 6x potency, Silicea (Silicic Acid or Silica)6x potency, Calc Sulph (Calcium Sulphate)6x potency

Inactive:

Cane Sugar Base to Preserve Product

Uses

Temporarily relieves gum discomfort, swollen and bleeding gums, pus pockets, and foul breath.*

*CLAIMS BASED ON TRADITIONAL HOMEOPATHIC PRACTICE, NOT ACCEPTED MEDICAL EVIDENCE, NOT FDA EVALUATED.

This product is not intended to diagnose, treat, cure, or prevent any disease.

Uses

Temporarily relieves gum discomfort, swollen and bleeding gums, pus pockets, and foul breath.*

*CLAIMS BASED ON TRADITIONAL HOMEOPATHIC PRACTICE, NOT ACCEPTED MEDICAL EVIDENCE, NOT FDA EVALUATED.

This product is not intended to diagnose, treat, cure, or prevent any disease.

KEEP OUT OF REACH OF CHILDREN

Warnings and Storage:

Ask a professional before use if pregnant or breastfeeding or if you have severe symptoms. Keep away from children. If you have a reaction to this product that is not positive, discontinue use. Store in a cool and dry place.

Warnings and Storage:

Ask a professional before use if pregnant or breastfeeding or if you have severe symptoms. Keep away from children. If you have a reaction to this product that is not positive, discontinue use. Store in a cool and dry place.

*CLAIMS BASED ON TRADITIONAL HOMEOPATHIC PRACTICE, NOT ACCEPTED MEDICAL EVIDENCE NOT FDA EVALUATED.

This product is not intended to diagnose, treat, cure, or prevent any disease.

Entire package label